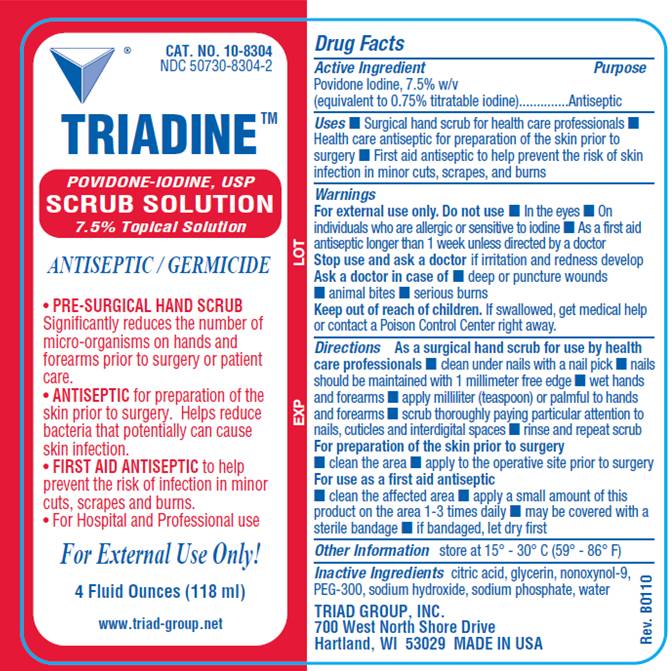 DRUG LABEL: Triadine Scrub
NDC: 50730-8304 | Form: SOLUTION
Manufacturer: Triad Group
Category: otc | Type: HUMAN OTC DRUG LABEL
Date: 20100419

ACTIVE INGREDIENTS: povidone-iodine .075 mL/1 mL
INACTIVE INGREDIENTS: citric acid monohydrate; glycerin; nonoxynol-9; polyethylene glycol 300; sodium hydroxide; sodium phosphate, monobasic, monohydrate; water

DRUG FACTS

ACTIVE INGREDIENT

Povidone Iodine, 7.5% w/v (equivalent to 0.75% titratable iodine)

PURPOSE

Antiseptic

USES

- Surgical hand scrub for health care professionals
- Health care antiseptic for preparation of the skin prior to surgery
- First aid antiseptic to help prevent the risk of infection in minor cuts, scrapes and burns

WARNINGS

For external use only.

Do not use

- in the eyes
- on individuals who are allergic or sensitive to iodine
- as a first aid antiseptic for longer than 1 week unless directed by a doctor

Ask a doctor in case of

- deep or puncture wounds
- animal bites
- serious burns

Stop use and ask a doctor

if irritation and redness develop

Keep out of reach of children

If swallowed, get medical help or contact a Poison Control Center right away.

DIRECTIONS

As a surgical hand scrub for use by health care professionals

- clean under nails with a nail pick
- nails should be maintained with 1 millimeter free edge
- wet hands and forearms
- apply milliliter (teaspoon) or palmful to hands and forearms
- scrub thoroughly paying particular attention to nails, cuticles and interdigital spaces
- rinse and repeat scrub

For preparation of the skin prior to surgery

- clean the affected area
- apply to the operative site prior to surgery

As a first aid antiseptic

- clean the affected area
- apply a small amount of this product to the area 1-3 times daily
- may be covered with a sterile bandage
- if bandaged, let dry first

OTHER INFORMATION

store at 15° - 30° C (59° - 86° F)

INACTIVE INGREDIENTS

citric acid, glycerin, nonoxynol-9, PEG-300, sodium hydroxide, sodium phosphate, water

LABEL INFORMATION

Cat. No. 10-8304
NDC 50730-8304-2
TRIADINE™

POVIDONE-IODINE, USP
SCRUB SOLUTION
7.5% Topical Solution
ANTISEPTIC / GERMICIDE

- PRE-SURGICAL HAND SCRUB. Significantly reduces the number of micro-organisms on hand and forearms prior to surgery or patient care.
- ANTISEPTIC for preparation of the skin prior to surgery. Helps reduce bacteria that potentially can cause skin infection.
- FIRST AID ANTISEPTIC to help prevent the risk of infection in minor cuts, scrapes and burns.

FOR EXTERNAL USE ONLY!
4 Fluid Ounces (118 ml)

www.triad-group.net

TRIAD GROUP, INC.
700 West North Shore Drive
Hartland, WI 53029
MADE IN USA